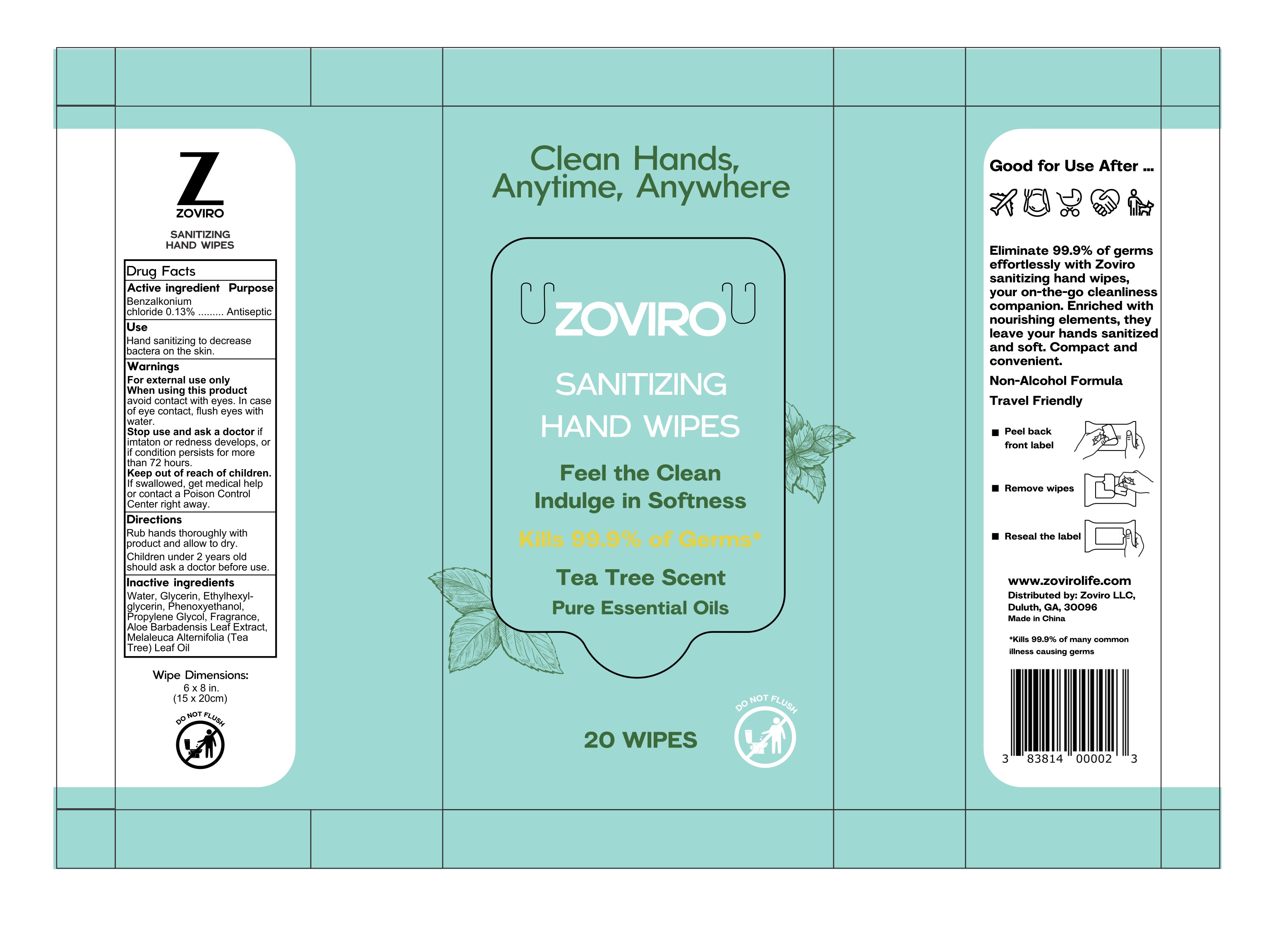 DRUG LABEL: Zoviro
NDC: 83814-001 | Form: SWAB
Manufacturer: Zoviro, LLC
Category: otc | Type: HUMAN OTC DRUG LABEL
Date: 20250326

ACTIVE INGREDIENTS: BENZALKONIUM CHLORIDE 0.13 g/100 g
INACTIVE INGREDIENTS: PROPYLENE GLYCOL; MELALEUCA ALTERNIFOLIA (TEA TREE) LEAF OIL; ETHYLHEXYLGLYCERIN; GLYCERIN; ALOE VERA LEAF; PHENOXYETHANOL; WATER

Zoviro Alcohol-Free Hand Sanitizing Wipes With Tea Tree Oil

Active ingredient

Benzalkonium chloride 0.13%

Purpose

Antiseptic

When using this product avoid contact with eyes. In case of eye contact, flush eyes with water.

Stop use and ask a doctor if imtaton or redness develops, or if condition persists for more than 72 hours.

Keep out of reach of children. If swallowed, get medical help or contact a Poison Control Center right away.

Inactive ingredients

Water, Glycerin, Ethylhexyl- glycerin, Phenoxyethanol, Propylene Glycol, Fragrance, Aloe Barbadensis Leaf Extract, Melaleuca Alternifolia (Tea Tree) Leaf Oil

Directions

Rub hands thoroughly with product and allow to dry. Children under 2 years old should ask a doctor before use.

Use

Hand sanitizing to decrease bactera on the skin.

Warnings

For external use only